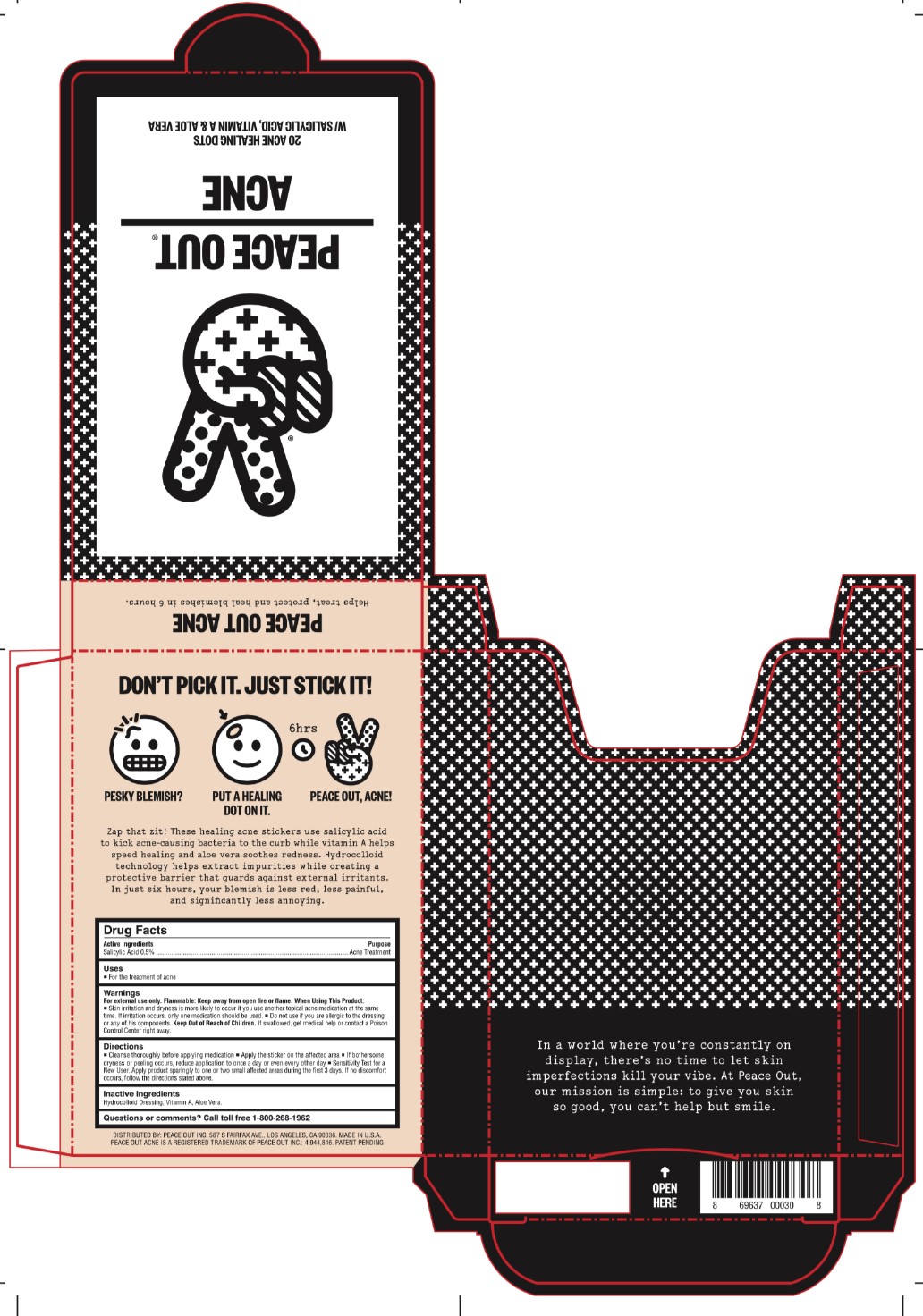 DRUG LABEL: Peace Out Acne
NDC: 71494-101 | Form: PATCH
Manufacturer: Peace Out LLC.
Category: otc | Type: HUMAN OTC DRUG LABEL
Date: 20241018

ACTIVE INGREDIENTS: SALICYLIC ACID 0.5 mg/1 1
INACTIVE INGREDIENTS: VITAMIN A; ALOE VERA LEAF

Peace Out Acne

Active Ingredients

Salicylic Acid 0.5%

Purpose

Acne Treatment

Uses

- For the treatment of acne

Warning

For external use only. Flammable: Keep away from open fire or flame. When Using This Product.

- Skin irritation and dryness is more likely to occur if you use another topical acne medication at the same time. If irritation occurs, only one medication should be used.
- Do not use if you are allergic to the dressing or any of his components.

- Keep Out of Reach of Children. If swallowed, get medical help or contact a Posion Control Center right away.

Directions

- Cleanse thoroughly before applying medication
- Apply the sticker on the affected area
- If bothersome dryness or peeling occurs, reduce application to once a day or even every other day
- Sensitivity Test for a New User. Apply product sparingly to one or two small affected areas during the first 3 days. If no discomfort occurs, follow the directions stated above.

Inactive Ingredients

Hydrocolloid Dressing, Vitamin A, Aloe Vera.

Questions of comments?

Call toll free 1-800-268-1962